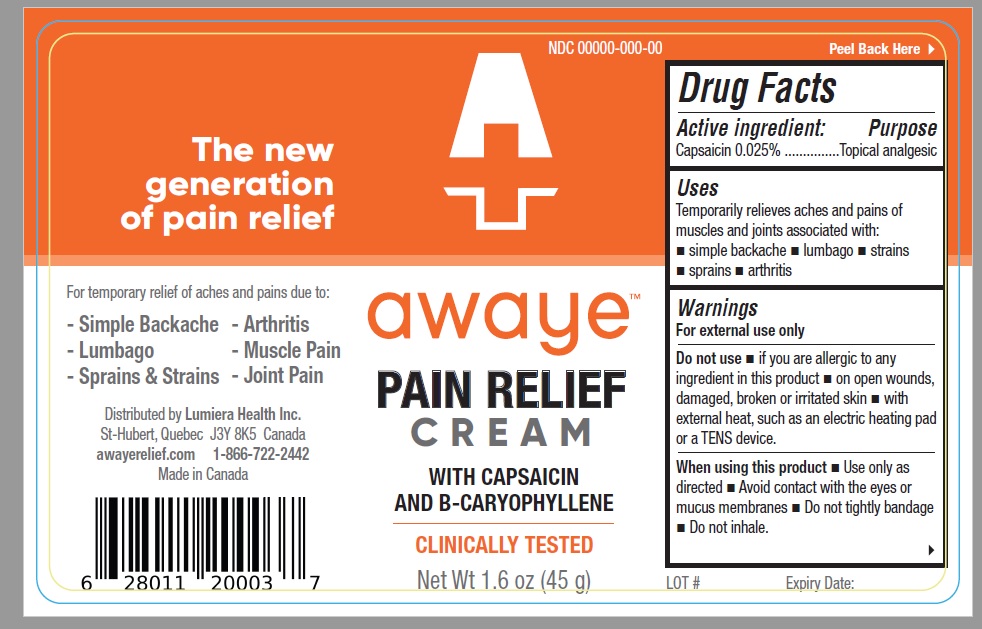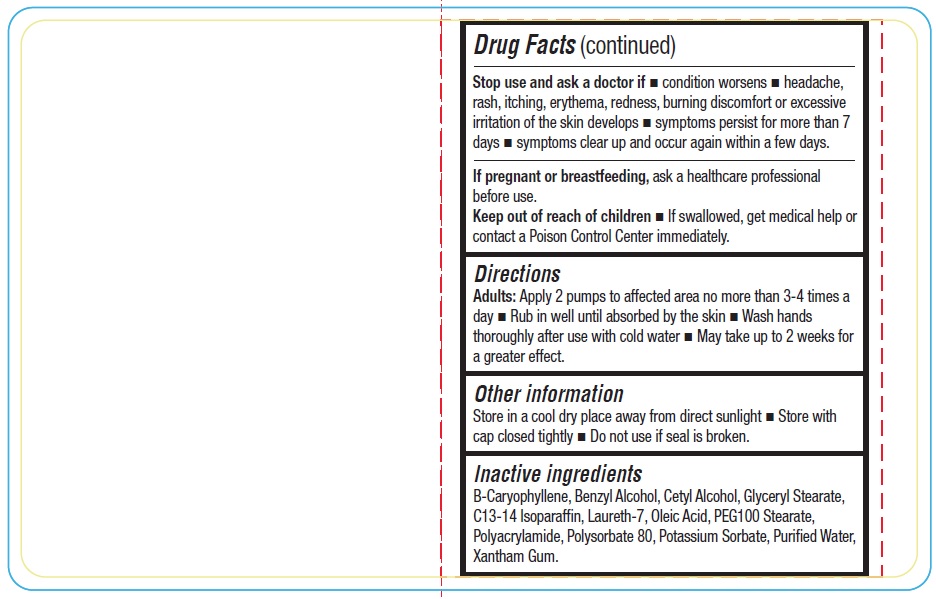 DRUG LABEL: Awaye
NDC: 82531-001 | Form: CREAM
Manufacturer: Lumiera Health Inc.
Category: otc | Type: HUMAN OTC DRUG LABEL
Date: 20220228

ACTIVE INGREDIENTS: CAPSAICIN 0.025 g/100 g
INACTIVE INGREDIENTS: CARYOPHYLLENE; BENZYL ALCOHOL; CETYL ALCOHOL; GLYCERYL MONOSTEARATE; C13-14 ISOPARAFFIN; LAURETH-7; OLEIC ACID; PEG-100 STEARATE; POLYACRYLAMIDE (1500 MW); POLYSORBATE 80; POTASSIUM SORBATE; WATER; XANTHAN GUM

Active ingredient Purpose

Capsaicin 0.025% Topical analgesic

Uses

Temporarily relieves aches and pains of muscles and joints associated with: simple backache – lumbago – strains – sprains - arthritis

Warning

For external use only
Flammable: Keep away from fire or flame and heated surfaces.
Do not use – if you are allergic to any ingredient in this product - on open wounds, damaged, broken or irritated skin - with external heat, such as an electric heating pad or a TENS device.
When using this product – Use only as directed - Avoid contact with the eyes or mucus membranes - Do not tightly bandage - Do not inhale.
Stop use and ask a doctor if – condition worsens – headache, rash, itching, erythema, redness, burning discomfort or excessive irritation of the skin develops - symptoms persist for more than 7 days – symptoms clear up and occur again within a few days.
If pregnant or breastfeeding, ask a healthcare professional before use.
Keep out of reach of children. If swallowed, get medical help or contact a Poison Control Center immediately.

Direction

Apply 2 pumps to affected area no more than 3-4 times a day - Rub in well until absorbed by the skin - wash hands thoroughly after use with cold water - May take up to 2 weeks for a greater effect.

Inactive ingredient

B-Caryophyllene, Benzyl Alcohol, Cetyl Alcohol, Glyceryl Stearate, C13-14 Isoparaffin, Laureth-7, Oleic Acid, PEG100 Stearate, Polyacrylamide, Polysorbate 80, Potassium Sorbate, Purified Water, Xantham Gum.

Other information

Store in a cool dry place away from direct sunlight – Store with cap closed tightly – Do not use if seal is broken.